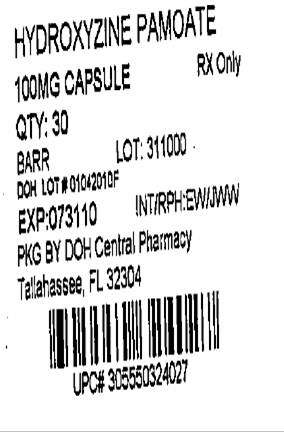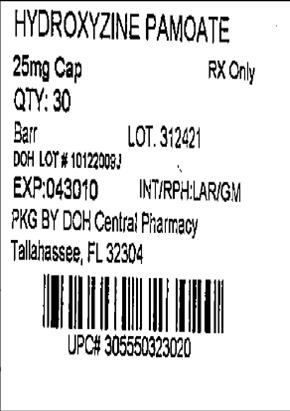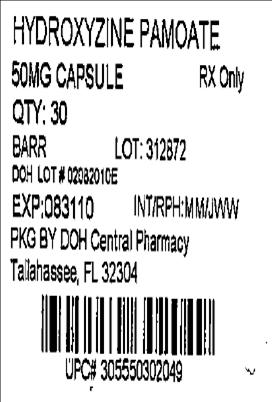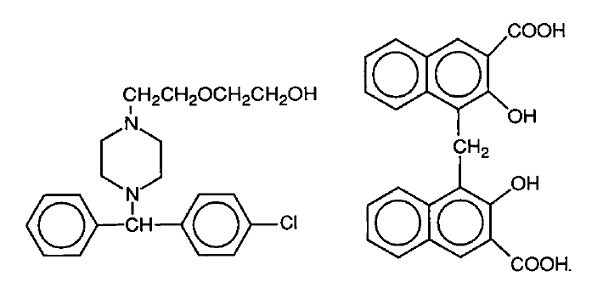 DRUG LABEL: Hydroxyzine Pamoate
NDC: 53808-0373 | Form: CAPSULE
Manufacturer: State of Florida DOH Central Pharmacy
Category: prescription | Type: HUMAN PRESCRIPTION DRUG LABEL
Date: 20100525

ACTIVE INGREDIENTS: HYDROXYZINE PAMOATE 25 mg/1 1
INACTIVE INGREDIENTS: ANHYDROUS LACTOSE; CROSCARMELLOSE SODIUM; ALCOHOL; MAGNESIUM STEARATE; STARCH, CORN

HYDROXYZINE PAMOATE CAPSULES, USP

Rx only

DESCRIPTION:

Hydroxyzine Pamoate is a light yellow, practically odorless powder, practically insoluble in water and methanol and freely soluble in dimethylformamide. It is chemically designated as 2-[2-[4-(p-chloro-α-p h e n y l b e n z y l) - 1 - p i p e r a z i n y l ] -ethoxy]ethanol 4,4’- methylenebis[3-hydroxy-2-naphthoate] (1:1) and can be structurally represented as follows:

C21H27CIN2O2•C23H16O6 Molecular Weight: 763.29

Hydroxyzine Pamoate Capsules produce an ataraxic effect and they are administered in doses equivalent to 25 mg, 50 mg or 100 mg of hydroxyzine HCl.

Inactive Ingredients:

Croscarmellose sodium, ethyl alcohol, magnesium stearate, and pregelatinized starch. The 25 mg also contains anhydrous lactose. The 50 mg and 100 mg also contain lactose monohydrate.

The capsule shell ingredients are D&C red no. 28, D&C yellow no. 10, gelatin, sodium lauryl sulfate, and titanium dioxide. The 25 mg capsule shell also contains benzyl alcohol, butylparaben, EDTA calcium disodium, FD&C blue no. 1, FD&C red no. 40, methylparaben, propylparaben, and sodium propionate. The 50 mg capsule shell also contains benzyl alcohol, butylparaben, D&C red no. 33, EDTA calcium disodium, methylparaben, propylparaben, and sodium propionate. The 100 mg capsule shell also contains FD&C blue no. 1, FD&C red no. 40, and silicon dioxide.

The imprinting ink contains pharmaceutical glaze, propylene glycol, SDA-3A alcohol, and synthetic black iron oxide. The imprinting ink on the 25 mg and 50 mg capsules also contain ammonium hydroxide, dimethylpolysiloxane, ethylene glycol monoethyl ether, and lecithin. The imprinting ink on the 100 mg capsule also contains n-butyl alcohol, D&C yellow no. 10 aluminum lake, FD&C blue no. 1 aluminum lake, FD&C blue no. 2 aluminum lake, and FD&C red no. 40 aluminum lake.

CLINICAL PHARMACOLOGY:

Hydroxyzine pamoate is unrelated chemically to the phenothiazines, reserpine, meprobamate, or the benzodiazepines.

Hydroxyzine pamoate is not a cortical depressant, but its action may be due to a suppression of activity in certain key regions of the subcortical area of the central nervous system. Primary skeletal muscle relaxation has been demonstrated experimentally. Bronchodilator activity, and antihistaminic and analgesic effects have been demonstrated experimentally and confirmed clinically. An antiemetic effect, both by the apomorphine test and the veriloid test, has been demonstrated. Pharmacological and clinical studies indicate that hydroxyzine in therapeutic dosage does not increase gastric secretion or acidity and in most cases has mild antisecretory activity. Hydroxyzine is rapidly absorbed from the gastrointestinal tract and clinical effects are usually noted within 15 to 30 minutes after oral administration.

INDICATIONS AND USAGE:

For symptomatic relief of anxiety and tension associated with psychoneurosis and as an adjunct in organic disease states in which anxiety is manifested.

Useful in the management of pruritus due to allergic conditions such as chronic urticaria and atopic and contact dermatoses, and in histamine-mediated pruritus.

As a sedative when used as a premedication and following general anesthesia, Hydroxyzine maypotentiate meperidine and barbiturates, so their use in pre-anesthetic adjunctive therapy should be modified on an individual basis. Atropine and other belladonna alkaloids are not affected by the drug. Hydroxyzine is not known to interfere with the action of digitalis in any way and it may be used concurrently with this agent.

The effectiveness of hydroxyzine as an antianxiety agent for long-term use, that is, more than 4 months, has not been assessed by systematic clinical studies. The physician should reassess periodically the usefulness of the drug for the individual patient.

CONTRAINDICATIONS:

Hydroxyzine, when administered to the pregnant mouse, rat, and rabbit, induced fetal abnormalities in the rat and mouse at doses substantially above the human therapeutic range. Clinical data in human beings are inadequate to establish safety in early pregnancy. Until such data are available, hydroxyzine is contraindicated in early pregnancy.

Hydroxyzine pamoate is contraindicated for patients who have shown a previous hypersensitivity to it.

WARNINGS:

Nursing Mothers:

It is not known whether this drug is excreted in human milk. Since many drugs are so excreted, hydroxyzine should not be given to nursing mothers.

PRECAUTIONS:

THE POTENTIATING ACTION OF HYDROXYZINE MUST BE CONSIDERED WHEN THE DRUG IS USED IN CONJUNCTION WITH CENTRAL NERVOUS SYSTEM DEPRESSANTS SUCH AS NARCOTICS, NON-NARCOTIC ANALGESICS, AND BARBITURATES. Therefore, when central nervous system depressants are administered concomitantly with hydroxyzine, their dosage should be reduced. Since drowsiness may occur with use of the drug, patients should be warned of this possibility and cautioned against driving a car or operating dangerous machinery while taking hydroxyzine pamoate. Patients should be advised against the simultaneous use of other CNS depressant drugs, and cautioned that the effect of alcohol may be increased.

Geriatric Use:

A determination has not been made whether controlled clinical studies of hydroxyzine pamoate included sufficient numbers of subjects aged 65 and over to define a difference in response from younger subjects. Other reported clinical experience has not identified differences in responses between the elderly and younger patients.

In general, dose selection for an elderly patient should be cautious, usually starting at the low end of the dosing range, reflecting the greater frequency of decreased hepatic, renal or cardiac function, and of concomitant disease or other drug therapy.

The extent of renal excretion of hydroxyzine pamoate has not been determined. Because elderly patients are more likely to have decreased renal function, care should be taken in dose selections.

Sedating drugs may cause confusion and over sedation in the elderly; elderly patients generally should be started on low doses of hydroxyzine pamoate and observed closely.

ADVERSE REACTIONS:

Side effects reported with the administration of hydroxyzine pamoate are usually mild and transitory in nature.

Anticholinergic:

Dry mouth.

Central Nervous System:

Drowsiness is usually transitory and may disappear in a few days of continued therapy or upon reduction of the dose. Involuntary motor activity, including rare instances of tremor and convulsions, has been reported, usually with doses considerably higher than those recommended. Clinically significant respiratory depression has not been reported at recommended doses.

Overdosage:

The most common manifestation of overdosage of hydroxyzine pamoate is hypersedation. As in the management of overdosage with any drug, it should be borne in mind that multiple agents may have been taken.

If vomiting has not occurred spontaneously, it should be induced. Immediate gastric lavage is also recommended. General supportive care, including frequent monitoring of the vital signs and close observation of the patient, is indicated. Hypotension, though unlikely, may be controlled with intravenous fluids and levarterenol or metaraminol. Do not use epinephrine, as hydroxyzine pamoate counteracts its pressor action. Caffeine and Sodium Benzoate Injection, USP, may be used to counteract central nervous system depressant effects.

There is no specific antidote. It is doubtful that hemodialysis would be of any value in the treatment of overdosage with hydroxyzine. However, if other agents such as barbiturates have been ingested concomitantly, hemodialysis may be indicated. There is no practical method to quantitate hydroxyzine in body fluids or tissue after its ingestion or administration.

DOSAGE AND ADMINISTRATION:

For symptomatic relief of anxiety and tension associated with psychoneurosis and as an adjunct in organic disease states in which anxiety is manifested: In adults, 50-100 mg q.i.d.; children under 6 years, 50 mg daily in divided doses and over 6 years, 50-100 mg daily in divided doses.

For use in the management of pruritus due to allergic conditions such as chronic urticaria and atopic and contact dermatoses, and in histamine-mediated pruritus: In adults, 25 mg t.i.d. or q.i.d.; children under 6 years, 50 mg daily in divided doses and over 6 years, 50-100 mg daily in divided doses.

As a sedative when used as a premedication and following general anesthesia: 50-100 mg in adults, and 0.6 mg/kg in children.

When treatment is initiated by the intramuscular route of administration, subsequent doses may be administered orally.

As with all medications, the dosage should be adjusted according to the patient’s response to therapy.

HOW SUPPLIED:

Hydroxyzine Pamoate Capsules, USP is equivalent to hydroxyzine hydrochloride.

25 mg: | Light yellow opaque cap/pink opaque body filled with yellow powder. Imprinted in black ink stylized barr over 323/25.

50 mg: | Light yellow opaque cap/maroon opaque body filled with yellow powder. Imprinted in black ink stylized barr over 302 /50.

100 mg: | Light yellow opaque cap/pink opaque body filled with yellow powder. Imprinted in black ink stylized barr over 324/100.

They are supplied by State of Florida DOH Central Pharmacy as follows:

NDC | Strength | Quantity/Form | Color | Source Prod. Code
53808-0373-1 | 25 mg | 30 Capsules in a Blister Pack | PINK | 0555-0323
53808-0374-1 | 50 mg | 30 Capsules in a Blister Pack | MAROON | 0555-0302
00555-0324-1 | 100 mg | 30 Capsules in a Blister Pack | PINK | 0555-0324

Dispense with a child-resistant closure in a well-closed container as defined in the USP/NF.

Store at controlled room temperature 15°-30°C (59°-86°F) [see USP].

MANUFACTURED BY

BARR LABORATORIES, INC.

POMONA, NY 10970

This Product was Repackaged By:

State of Florida DOH Central Pharmacy
104-2 Hamilton Park Drive
Tallahassee, FL 32304
United States